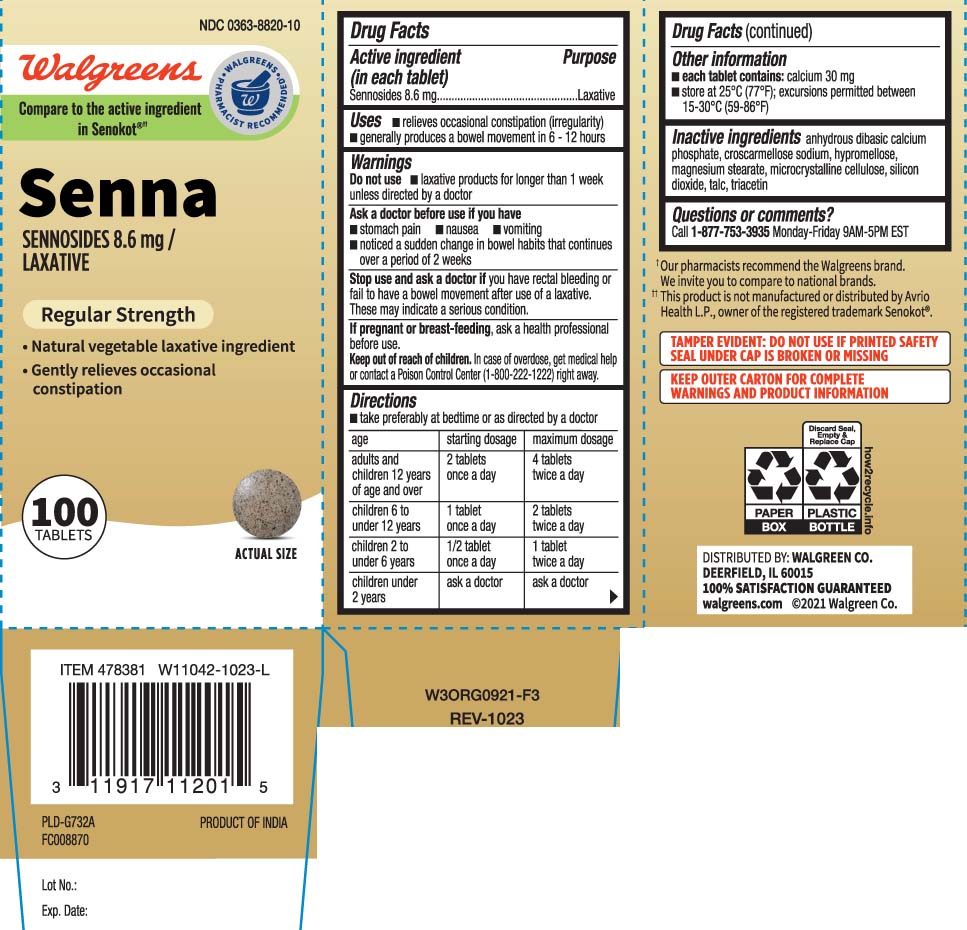 DRUG LABEL: Senna
NDC: 0363-8820 | Form: TABLET
Manufacturer: Walgreens
Category: otc | Type: HUMAN OTC DRUG LABEL
Date: 20250815

ACTIVE INGREDIENTS: SENNOSIDES 8.6 mg/1 1
INACTIVE INGREDIENTS: CROSCARMELLOSE SODIUM; DIBASIC CALCIUM PHOSPHATE DIHYDRATE; HYPROMELLOSES; MAGNESIUM STEARATE; CELLULOSE, MICROCRYSTALLINE; SILICON DIOXIDE; TALC; TRIACETIN

Drug Facts

Active ingredient (in each tablet)

Sennosides 8.6 mg

Purpose

Laxative

Uses

- relieves occasional constipation (irregularity)
- generally produces a bowel movement within 6- 12 hours.

Warnings

Do not use

- laxative products for longer than 1 week unless directed by a doctor

Ask a doctor before use if you have

- stomach pain
- nausea
- vomiting
- noticed a sudden change in bowel habits that continues over a period of 2 weeks.

Stop use and ask a doctor if

you have rectal bleeding or fail to have a bowel movement after use of a laxative. These may indicate a serious condition.

If pregnant or breast-feeding,

ask a health professional before use.

Keep out of reach of children.

In case of overdose, get medical help or contact a Poison Control Center (1-800-222-1222) right away.

Directions

- take preferably at bedtime or as directed by a doctor

age | starting dosage | maximum dosage
adults and children 12 years of age and over | 2 tablets once a day | 4 tablets twice a day
children 6 to under 12 years | 1 tablet once a day | 2 tablets twice a day
children 2 to under 6 years | 1/2 tablets once a day | 1 tablet twice a day
children under 2 years | ask a doctor | ask a doctor

Other information

- each tablet contains: calcium 30 mg
- store at 25o C (77o F); excursions permitted between 15-30ºC (59-86ºF)

Inactive Ingredients

anhydrous dibasic calcium phosphate, croscarmellose sodium, hypromellose, magnesium stearate, microcrystalline cellulose, silicon dioxide, talc, triacetin

Questions or comments?

Call 1-877-753-3935 Monday-Friday 9AM-5PM EST

Principal Display Panel

Compare to the active ingredient in Senokot®††

Senna

SENNOSIDES 8.6 mg/LAXATIVE

Regular Strength

- Natural vegetable laxative ingredient
- Gently relieves occasional constipation

TABLETS

††This product is not manufactured or distributed by Atlantis Consumer Healthcare Inc., owner of the registered trademark Senokot®.

TAMPER EVIDENT: DO NOT USE IF PRINTED SAFETY SEAL UNDER CAP IS BROKEN OR MISSING

KEEP OUTER CARTON FOR COMPLETE WARNINGS AND PRODUCT INFORMATION

DISTRIBUTED BY: WALGREEN CO.

DEERFIELD, IL 60015

Product Label

Walgreens Senna Regular Strength Laxative Tablets